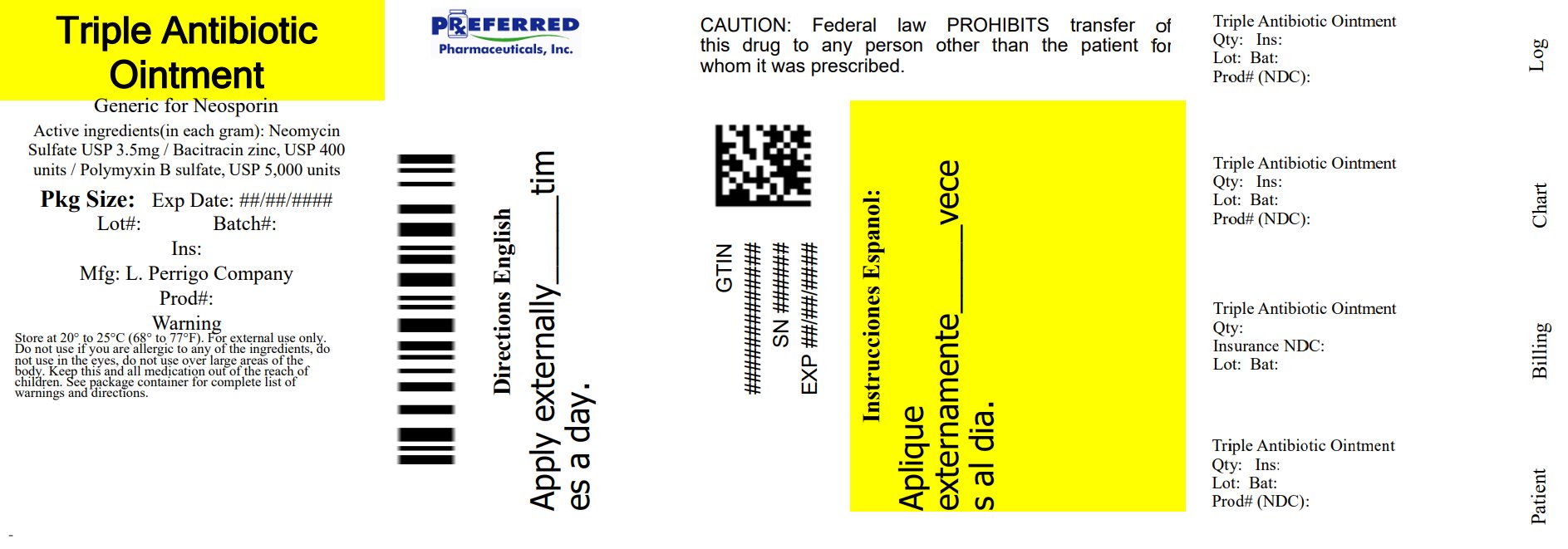 DRUG LABEL: Good Sense First Aid Antibiotic
NDC: 68788-8270 | Form: OINTMENT
Manufacturer: Preferred Pharmaceuticals Inc.
Category: otc | Type: HUMAN OTC DRUG LABEL
Date: 20251001

ACTIVE INGREDIENTS: BACITRACIN ZINC 400 [USP'U]/1 g; NEOMYCIN SULFATE 3.5 mg/1 g; POLYMYXIN B SULFATE 5000 [USP'U]/1 g
INACTIVE INGREDIENTS: PETROLATUM; COCOA BUTTER; COTTONSEED OIL; OLIVE OIL; SODIUM PYRUVATE; .ALPHA.-TOCOPHEROL ACETATE

Perrigo First Aid Antibiotic Drug Facts

Active ingredients (in each gram)

Bacitracin zinc equivalent to 400 units bacitracin

Neomycin sulfate equivalent to 3.5 mg of neomycin base

Polymyxin B 5,000 units as polymyxin B sulfate

Purpose

First aid antibiotic

Use

first aid to help prevent infection in minor:

- cuts
- scrapes
- burns

Warnings

For external use only.

Do not use

- if you are allergic to any of the ingredients
- in the eyes
- over large areas of the body

Ask a doctor before use if you have

- deep or puncture wounds
- animal bites
- serious burns

Stop use and ask a doctor if

- you need to use longer than 1 week
- condition persists or gets worse
- rash or other allergic reaction develops

Keep out of reach of children.

If swallowed, get medical help or contact a Poison Control Center right away. (1-800-222-1222)

Directions

- clean the affected area
- apply a small amount of this product (an amount equal to the surface area of the tip of a finger) on the area 1 to 3 times daily
- may be covered with a sterile bandage

Other information

- store at 20-25°C (68-77°F)

Inactive ingredients

cocoa butter, cottonseed oil, olive oil, sodium pyruvate, tocopheryl acetate, white petrolatum

Questions or comments?

1-800-719-9260

Principal Display Panel

Original Ointment

Triple Antibiotic

Long Lasting Infection Protection

Helps skin heal to look healthy

DOCTOR RECOMMENDED #1 combination of active ingredients

Original Ointment

First Aid Antibiotic

Bacitracin Zinc – Neomycin Sulfate – Polymyxin B Sulfate

Compare to active ingredients of Neosporin®

100% SATISFACTION GUARANTEED

NET WT 0.5 OZ (14 g)

Relabeled By: Preferred Pharmaceuticals Inc.

NDC 68788-8270-2